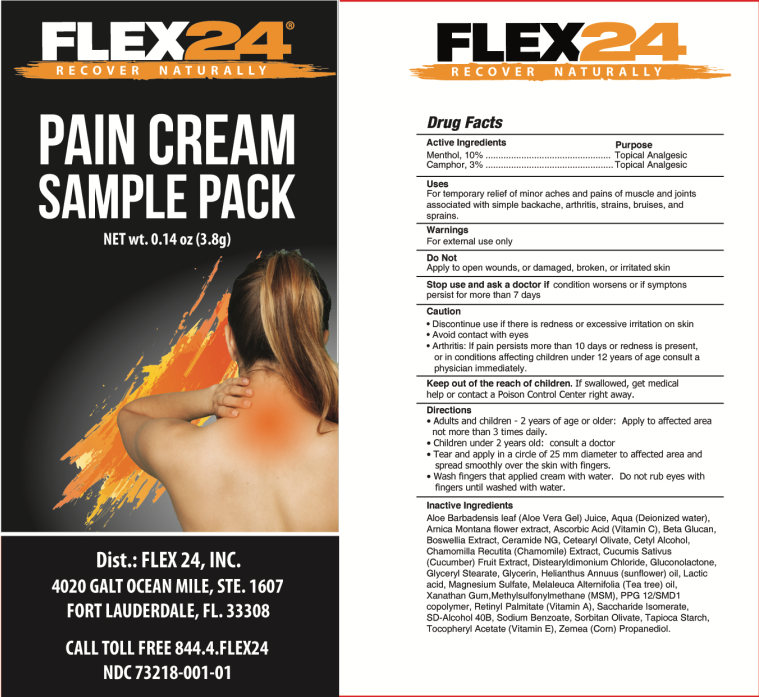 DRUG LABEL: Flex24 Pain
NDC: 73218-001 | Form: CREAM
Manufacturer: Flex24, Inc.
Category: otc | Type: HUMAN OTC DRUG LABEL
Date: 20220126

ACTIVE INGREDIENTS: CAMPHOR (NATURAL) 3 g/100 g; MENTHOL 10 g/100 g
INACTIVE INGREDIENTS: ALOE VERA LEAF; WATER; ARNICA MONTANA FLOWER; ASCORBIC ACID; GLUCAN ENDO-1,3-.ALPHA.-GLUCOSIDASE AGN1; BOSWELLIA SERRATA WHOLE; CERAMIDE NG; CETEARYL OLIVATE; CETYL ALCOHOL; MATRICARIA CHAMOMILLA; CUCUMIS SATIVUS WHOLE; DISTEARYLDIMONIUM CHLORIDE; GLUCONOLACTONE; GLYCERIN; HELIANTHUS ANNUUS WHOLE; LACTIC ACID; MAGNESIUM SULFATE ANHYDROUS; MELALEUCA ALTERNIFOLIA WHOLE; XANTHAN GUM; DIMETHYL SULFONE; PPG-12/SMDI COPOLYMER; VITAMIN A; SACCHARIDE ISOMERATE; ALCOHOL; denatonium benzoate; tert-butyl alcohol; SODIUM BENZOATE; SORBITAN OLIVATE; STARCH, TAPIOCA; .ALPHA.-TOCOPHEROL ACETATE, D-; PROPANEDIOL

Active Ingredients

Menthol, 10%

Camphor, 3%

Purpose

Topical Analgesic

Uses

For temporary relief of minor aches and pains of muscle and joints associated with simple backache, arthritis, strains, bruises, and sprains

Warnings

For external use only

Do not

Apply to open wounds, or damaged, broken, or irritated skin

Stop use and ask a doctor if

conditions worsens or if symptoms persist for more than 7 days

Caution

- Discontinue use if there is redness or excessive irritation on skin
- Avoid contact with eyes
- Arthritis: If pain persists more than 10 days or redness is present, or in conditions affecting children under 12 years of age, consult a physician immediately

KEEP OUT OF REACH OF CHILDREN

Keep out of the reach of children. If swallowed, get medical help or contact a Poison Control Center right away.

Directions

- Adults and children 2 years of age and older: Apply to the affected area not more than 3 times daily
- Children under 2 years old: consult a doctor
- Tear and apply in a circle of 25 mm diameter to affected area and spread smoothly over the skin with fingers
- Wash fingers that applied cream with water. Do not rub eyes with fingers until washed with water

Inactive Ingredients

Aloe Barbadensis leaf (Aloe Vera Gel) Juice, Aqua (Deionized water), Arnica Montana flower extract, Ascorbic Acid (Vitamin C), Beta Glucan, Boswellia Extract, Ceramide NG, Cetearyl Olivate, Cetyl Alcohol, Chamomilla Recutita (Chamomile) Extract, Cucumis Sativus (Cucumber) Fruit Extract, Distearyldimonium Chloride, Gluconolactone, Glyceryl Stearate, Glycerin, Helianthus Annuus (sunflower) oil, Lactic acid, Magnesium Sulfate, Melaleuca Alternifolia (Tea tree) oil, Xanathan Gum, Methylsulfonylmethane (MSM), PPG 12/SMD1 copolymer, Retinyl Palmitate (Vitamin A), Saccharide Isomerate, SD-Alcohol 40B, Sodium Benzoate, Sorbitan Olivate, Tapioca Starch, Tocopheryl Acetate (Vitamin E), Zemea (Corn) Propanediol

PACKAGE LABEL

FLEX24

RECOVER NATURALLY

PAIN CREAM

SAMPLE PACK

NET wt. 0.14 oz (3.8g)

Dist: FLEX24, INC.

4020 GALT OCEAN DRIVE, STE. 1607

FORT LAUDERDALE, FL 33308

CALL TOLL FREE 844.4.FLEX24

NDC 73218-001-01